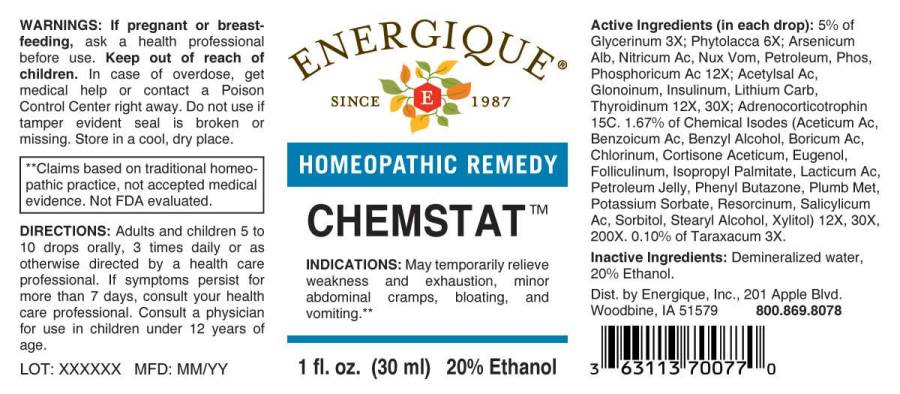 DRUG LABEL: Chemstat
NDC: 44911-0556 | Form: LIQUID
Manufacturer: Energique, Inc.
Category: homeopathic | Type: HUMAN OTC DRUG LABEL
Date: 20241024

ACTIVE INGREDIENTS: GLYCERIN 3 [hp_X]/1 mL; TARAXACUM OFFICINALE 3 [hp_X]/1 mL; PHYTOLACCA AMERICANA ROOT 6 [hp_X]/1 mL; ARSENIC TRIOXIDE 12 [hp_X]/1 mL; NITRIC ACID 12 [hp_X]/1 mL; STRYCHNOS NUX-VOMICA SEED 12 [hp_X]/1 mL; KEROSENE 12 [hp_X]/1 mL; PHOSPHORIC ACID 12 [hp_X]/1 mL; PHOSPHORUS 12 [hp_X]/1 mL; ASPIRIN 12 [hp_X]/1 mL; NITROGLYCERIN 12 [hp_X]/1 mL; INSULIN HUMAN 12 [hp_X]/1 mL; LITHIUM CARBONATE 12 [hp_X]/1 mL; THYROID 12 [hp_X]/1 mL; ACETIC ACID 12 [hp_X]/1 mL; BENZOIC ACID 12 [hp_X]/1 mL; BENZYL ALCOHOL 12 [hp_X]/1 mL; BORIC ACID 12 [hp_X]/1 mL; CHLORINE 12 [hp_X]/1 mL; CORTISONE ACETATE 12 [hp_X]/1 mL; EUGENOL 12 [hp_X]/1 mL; ESTRONE 12 [hp_X]/1 mL; ISOPROPYL PALMITATE 12 [hp_X]/1 mL; LACTIC ACID, DL- 12 [hp_X]/1 mL; POTASSIUM SORBATE 12 [hp_X]/1 mL; PETROLATUM 12 [hp_X]/1 mL; PHENYLBUTAZONE 12 [hp_X]/1 mL; LEAD 12 [hp_X]/1 mL; RESORCINOL 12 [hp_X]/1 mL; SALICYLIC ACID 12 [hp_X]/1 mL; STEARYL ALCOHOL 12 [hp_X]/1 mL; SORBITOL 12 [hp_X]/1 mL; XYLITOL 12 [hp_X]/1 mL; CORTICOTROPIN 15 [hp_C]/1 mL
INACTIVE INGREDIENTS: WATER; ALCOHOL

DRUG FACTS:

ACTIVE INGREDIENTS:

(in each drop): 5% of Glycerinum 3X; Phytolacca Decandra 6X; Arsenicum Album 12X, Nitricum Acidum 12X, Nux Vomica 12X, Petroleum 12X, Phosphorus 12X, Phosphoricum Acidum 12X; Acetylsalicylicum Acidum 12X, 30X, Glonoinum 12X, 30X, Insulinum (Human) 12X, 30X, Lithium Carbonicum 12X, 30X, Thyroidinum (Suis) 12X, 30X; Adrenocorticotrophin 15C. 1.67% of Aceticum Acidum 12X, 30X, 200X, Benzoicum Acidum 12X, 30X, 200X, Benzyl Alcohol 12X, 30X, 200X, Boricum Acidum 12X, 30X, 200X, Chlorinum 12X, 30X, 200X, Cortisone Aceticum 12X, 30X, 200X, Eugenol 12X, 30X, 200X, Folliculinum 12X, 30X, 200X, Isopropyl Palmitate 12X, 30X, 200X, Lacticum Acidum 12X, 30X, 200X, Petroleum Jelly 12X, 30X, 200X, Phenyl Butazone 12X, 30X, 200X, Plumbum Metallicum 12X, 30X, 200X, Potassium Sorbate 12X, 30X, 200X, Resorcinum 12X, 30X, 200X, Salicylicum Acidum 12X, 30X, 200X, Sorbitol 12X, 30X, 200X, Stearyl Alcohol 12X, 30X, 200X, Xylitol 12X, 30X, 200X. 0.10% of Taraxacum Officinale 3X.

INDICATIONS:

May temporarily relieve weakness and exhaustion, minor abdominal cramps, bloating, and vomiting.**

**Claims based on traditional homeopathic practice, not accepted medical evidence. Not FDA evaluated.

WARNINGS:

If pregnant or breastfeeding, ask a health professional before use.

Keep out of reach of children. In case of overdose, get medical help or contact a Poison Control Center right away.

Do not use if tamper evident seal is broken or missing.

Store in a cool, dry place.

Keep out of reach of children. In case of overdose, get medical help or contact a Poison Control Center right away.

DIRECTIONS:

Adults and children 5 to 10 drops orally, 3 times daily or as otherwise directed by a health care professional. If symptoms persist for more than 7 days, consult your health care professional. Consult a physician for use in children under 12 years of age.

INDICATIONS:

May temporarily relieve weakness and exhaustion, minor abdominal cramps, bloating, and vomiting.**

**Claims based on traditional homeopathic practice, not accepted medical evidence. Not FDA evaluated.

INACTIVE INGREDIENTS:

Demineralized water, 20% Ethanol.

QUESTIONS:

Dist. by Energique, Inc.

201 Apple Blvd.

Woodbine, IA 51579 800.869.8078

PACKAGE LABEL DISPLAY:

ENERGIQUE

SINCE 1987

HOMEOPATHIC REMEDY

CHEMSTAT

1 fl. oz. (30 ml)